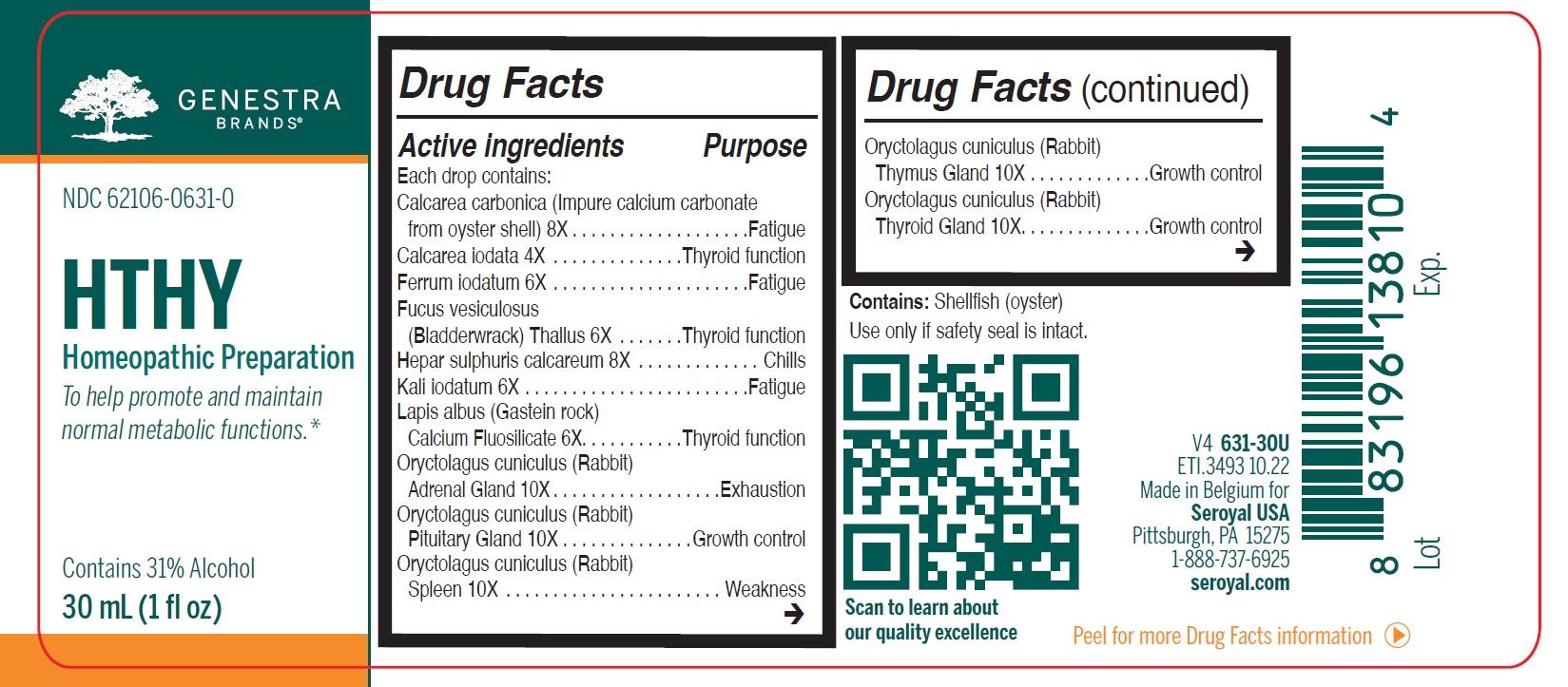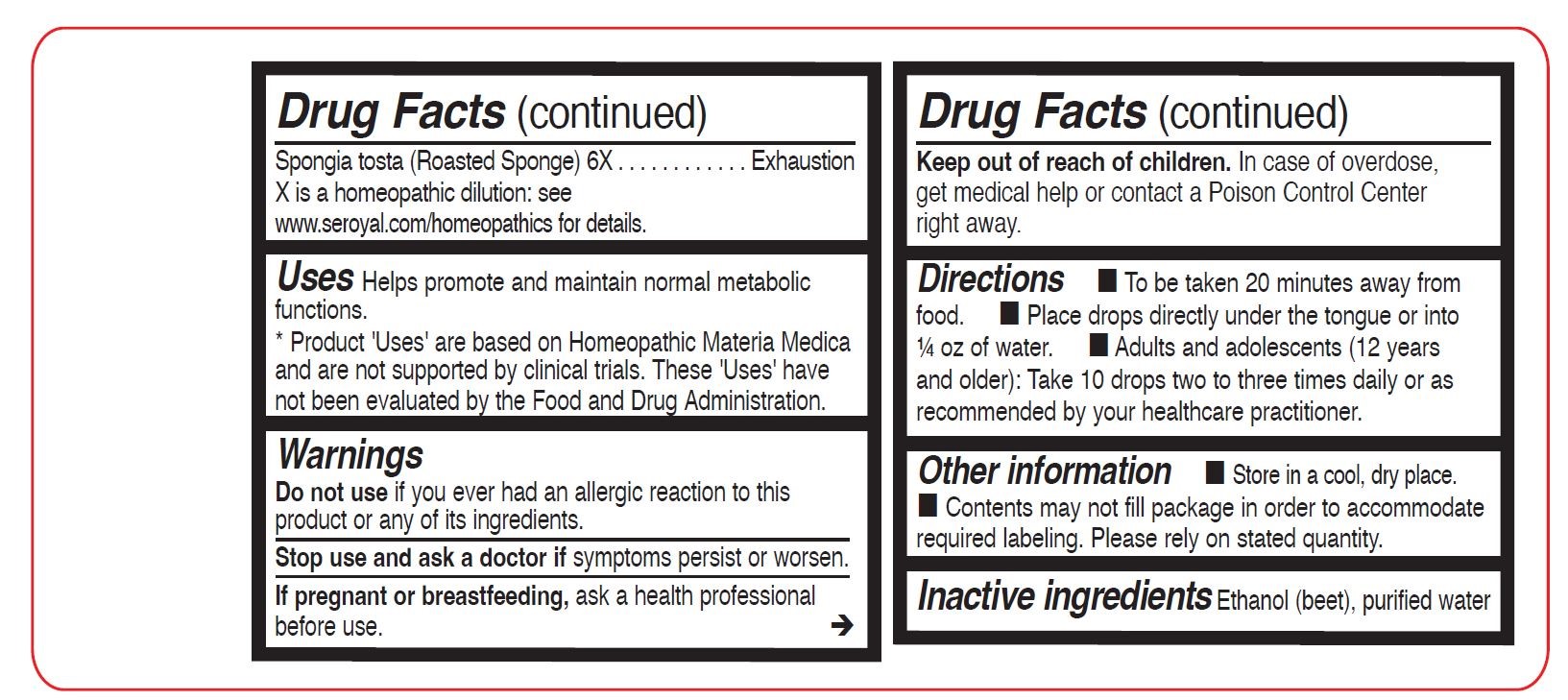 DRUG LABEL: HTHY
NDC: 62106-0631 | Form: LIQUID
Manufacturer: Seroyal USA
Category: homeopathic | Type: HUMAN OTC DRUG LABEL
Date: 20230130

ACTIVE INGREDIENTS: OYSTER SHELL CALCIUM CARBONATE, CRUDE 8 [hp_X]/30 mL; CALCIUM IODIDE 4 [hp_X]/30 mL; FERROUS IODIDE 6 [hp_X]/30 mL; FUCUS VESICULOSUS 6 [hp_X]/30 mL; CALCIUM SULFIDE 8 [hp_X]/30 mL; CALCIUM HEXAFLUOROSILICATE 6 [hp_X]/30 mL; ORYCTOLAGUS CUNICULUS ADRENAL GLAND 10 [hp_X]/30 mL; ORYCTOLAGUS CUNICULUS PITUITARY GLAND 10 [hp_X]/30 mL; ORYCTOLAGUS CUNICULUS SPLEEN 10 [hp_X]/30 mL; ORYCTOLAGUS CUNICULUS THYMUS 10 [hp_X]/30 mL; SPONGIA OFFICINALIS SKELETON, ROASTED 6 [hp_X]/30 mL; POTASSIUM IODIDE 6 [hp_X]/30 mL; ORYCTOLAGUS CUNICULUS THYROID 10 [hp_X]/30 mL
INACTIVE INGREDIENTS: WATER; ALCOHOL

HTHY

Active ingredients

Each drop contains:
Calcarea carbonica 8X
Calcarea iodata 4X
Ferrum iodatum 6X
Fucus vesiculosus (Bladderwrack) Thallus 6X
Hepar sulphuris calcareum 8X
Kali iodatum 6X
Lapis albus (Gastein rock) Calcium Fluosilicate 6X
Oryctolagus cuniculus (Rabbit) Adrenal Gland 10X
Oryctolagus cuniculus (Rabbit) Pituitary Gland 10X

Oryctolagus cuniculus (Rabbit) Spleen 10X
Oryctolagus cuniculus (Rabbit) Thymus Gland 10X

Oryctolagus cuniculus (Rabbit) Thyroid Gland 10X
Spongia tosta (Roasted Sponge) 6X

Uses

Helps promote and maintain normal metabolic functions.

Warnings
Stop use and ask a doctor if symptoms persist or worsen.
If pregnant or breastfeeding, ask a health professional before use.
Keep out of reach of children.
In case of overdose, get medical help or contact a Poison Control Center right away.

Contains: Shellfish (oyster)

Stop use and ask a doctor if symptoms persist or worsen.

PREGNANCY OR BREAST FEEDING

If pregnant or breastfeeding, ask a health professional before use.

Keep out of reach of children.

OVERDOSAGE

In case of overdose, get medical help or contact a Poison Control Center right away.

Other information

Store in a cool, dry place.

Use only if safety seal is intact.

Contents may not fill package in order to accommodate required labeling. Please rely on stated quantity.

Inactive ingredients

Ethanol (beet), purified water

Directions

To be taken 20 minutes away from food.

Place drops directly under the tongue or into ¼ oz of water.

Adults and adolescents (12 years and older): Take 10 drops two to three times daily or as recommended
by your healthcare practitioner.

Children (under 12 years): Take under the direction of your healthcare practitioner.

Uses

Helps promote and maintain normal metabolic functions.

Directions

To be taken 20 minutes away from food.

Place drops directly under the tongue or into ¼ oz of water.

Adults and adolescents (12 years and older): Take 10 drops two to three times daily or as recommended
by your healthcare practitioner.

Children (under 12 years): Take under the direction of your healthcare practitioner.

PACKAGE LABEL

Genestra Brands

NDC 62106-0631-0

HTHY

HOMEOPATHIC PREPARATION

To help promote and maintain normal metabolic functions.

Contains 31% Alcohol

1 fl oz (30 mL)